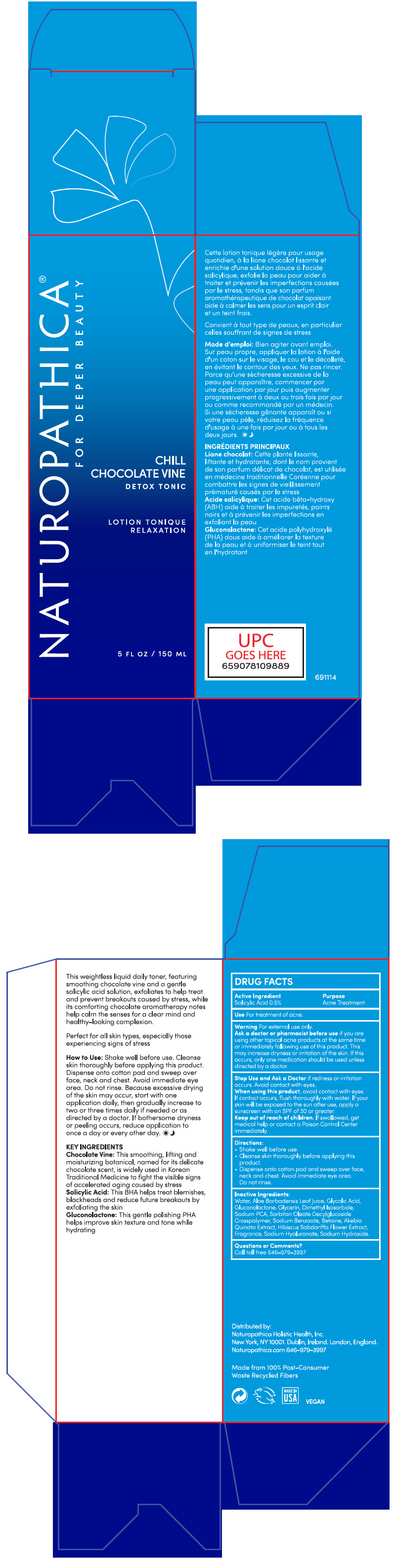 DRUG LABEL: NATUROPATHICA CHILL CHOCOLATE VINE DETOX TONIC
NDC: 64657-005 | Form: LOTION
Manufacturer: Naturopathica Holistic Health
Category: otc | Type: HUMAN OTC DRUG LABEL
Date: 20211130

ACTIVE INGREDIENTS: Salicylic Acid 0.5 g/100 mL
INACTIVE INGREDIENTS: Water; Aloe Vera Leaf; Glycolic Acid; Gluconolactone; Glycerin; Dimethyl Isosorbide; Sodium Pyrrolidone Carboxylate; Sodium Benzoate; Betaine; Hibiscus Sabdariffa Flower; Hyaluronate Sodium; Sodium Hydroxide

NATUROPATHICA® CHILL CHOCOLATE VINE DETOX TONIC

Drug Facts

Active Ingredient

Salicylic Acid 0.5%

Purpose

Acne Treatment

Use

For treatment of acne

Warning

For external use only

Ask a doctor or pharmacist before use if you are using other topical acne products at the same time or immediately following use of this product. This may increase dryness or irritation of the skin. If this occurs, only one medication should be used unless directed by a doctor.

Stop Use and Ask a Doctor if redness or irritation occurs. Avoid contact with eyes.

When using this product, avoid contact with eyes. If contact occurs, flush thoroughly with water. If your skin will be exposed to the sun after use, apply a sunscreen with an SPF of 30 or greater.

Keep out of reach of children. If swallowed, get medical help or contact a Poison Control Center immediately.

Directions

- Shake well before use.
- Cleanse skin thoroughly before applying this product.
- Dispense onto cotton pad and sweep over face, neck and chest. Avoid immediate eye area. Do not rinse.

Inactive Ingredients

Water, Aloe Barbadensis Leaf Juice, Glycolic Acid, Gluconolactone, Glycerin, Dimethyl Isosorbide, Sodium PCA, Sorbitan Oleate Decylglucoside Crosspolymer, Sodium Benzoate, Betaine, Akebia Quinata Extract, Hibiscus Sabdariffa Flower Extract, Fragrance, Sodium Hyaluronate, Sodium Hydroxide.

Questions or Comments?

Call toll free 646-979-3997

Distributed by:
Naturopathica Holistic Health, Inc.
New York, NY 10001. Dublin, Ireland. London, England.

PRINCIPAL DISPLAY PANEL - 150 ML Bottle Carton

NATUROPATHICA®
FOR DEEPER BEAUTY

CHILL
CHOCOLATE VINE
DETOX TONIC

LOTION TONIQUE
RELAXATION

5 FL OZ / 150 ML